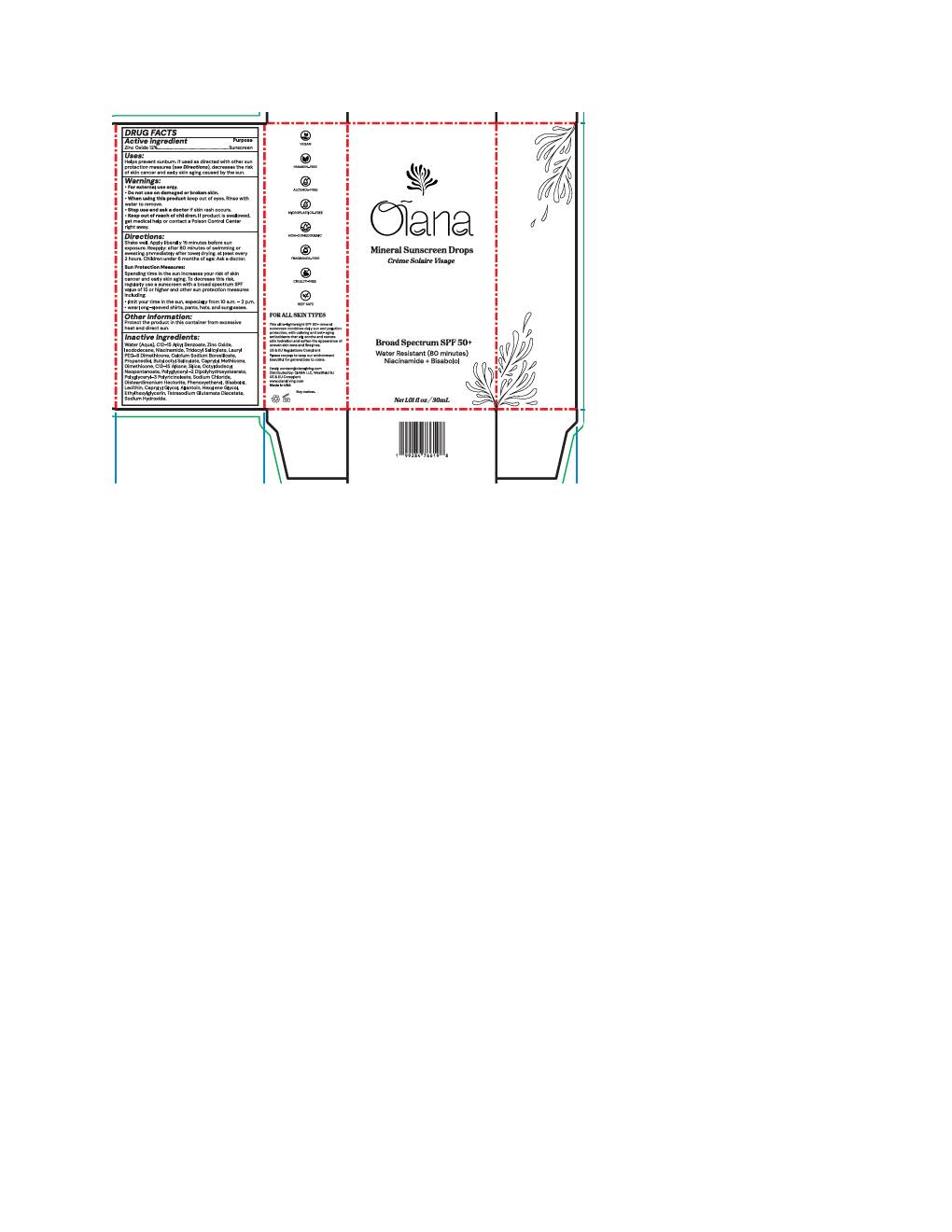 DRUG LABEL: Oiana Mineral Sunscreen Drops
NDC: 87342-2368 | Form: LOTION
Manufacturer: Oiana LLC
Category: otc | Type: HUMAN OTC DRUG LABEL
Date: 20260114

ACTIVE INGREDIENTS: ZINC OXIDE 132 mg/1 mL
INACTIVE INGREDIENTS: SILICON DIOXIDE; POLYGLYCERYL-2 DIPOLYHYDROXYSTEARATE; LECITHIN, SOYBEAN; DIMETHICONE 200; ALKYL (C12-15) BENZOATE; .ALPHA.-BISABOLOL, (+)-; LAURYL PEG-8 DIMETHICONE (300 CPS); BUTYLOCTYL SALICYLATE; OCTYLDODECYL NEOPENTANOATE; ISODODECANE; WATER; NIACINAMIDE; ETHYLHEXYLGLYCERIN; HEXYLENE GLYCOL; PROPANEDIOL; TETRASODIUM GLUTAMATE DIACETATE; SODIUM CHLORIDE; PHENOXYETHANOL; ALLANTOIN; TRIDECYL SALICYLATE; CAPRYLYL METHICONE; C13-15 ALKANE; SODIUM HYDROXIDE; CALCIUM SODIUM BOROSILICATE; DISTEARDIMONIUM HECTORITE; CAPRYLYL GLYCOL

Oiana Mineral Sunscreen Drops